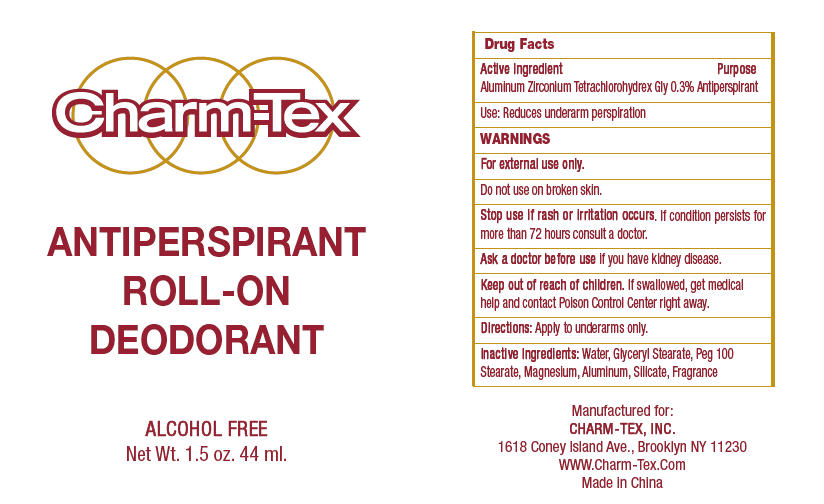 DRUG LABEL: Charm-Tex 
NDC: 40057-6001 | Form: GEL
Manufacturer: Charm-Tex, Inc
Category: otc | Type: HUMAN OTC DRUG LABEL
Date: 20120301

ACTIVE INGREDIENTS: ALUMINUM ZIRCONIUM TETRACHLOROHYDREX GLY 0.3 mL/100 mL
INACTIVE INGREDIENTS: Water; Glyceryl Monostearate; Peg-100 Stearate; Magnesium; Aluminum

ANTIPERSPIRANT ROLL-ON DEODORANT

Drug Facts

Active Ingredient

Aluminum Zirconium Tetrachlorohydrex Gly 0.3%

Purpose

Antiperspirant

Use

Reduces underarm perspiration

WARNINGS

For external use only.

Do not use on broken skin.

Stop use if rash or irritation occurs. If condition persists for more than 72 hours consult a doctor.

Ask a doctor before use if you have kidney disease.

Keep out of reach of children. If swallowed, get medical help and contact Poison Control Center right away.

Directions

Apply to underarms only.

Inactive Ingredients

Water, Glyceryl Stearate, Peg 100 Stearate, Magnesium, Aluminum, Silicate, Fragrance

Manufactured for:
CHARM-TEX, INC.
1618 Coney Island Ave., Brooklyn NY 11230

PRINCIPAL DISPLAY PANEL - 44 ml label

Charm-Tex

ANTIPERSPIRANT
ROLL-ON
DEODORANT

ALCOHOL FREE

Net Wt. 1.5 oz. 44 ml.